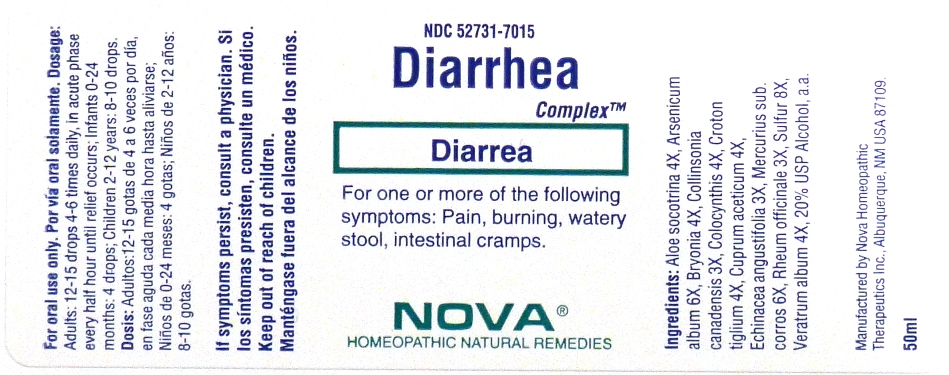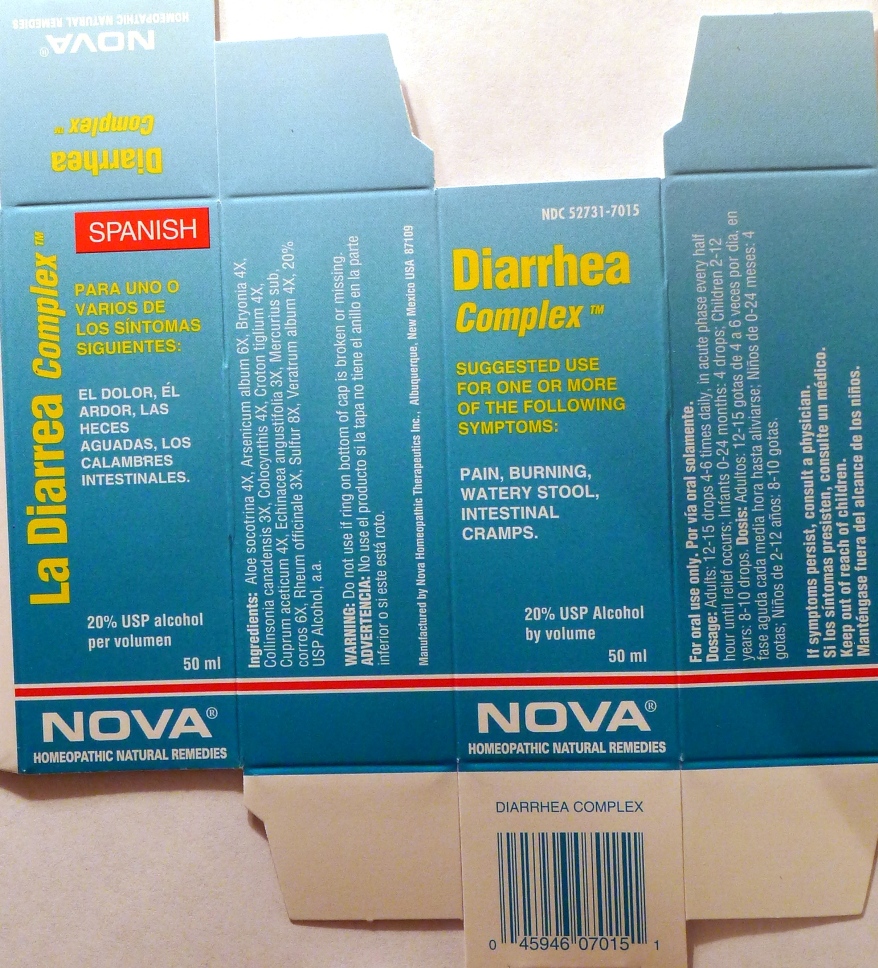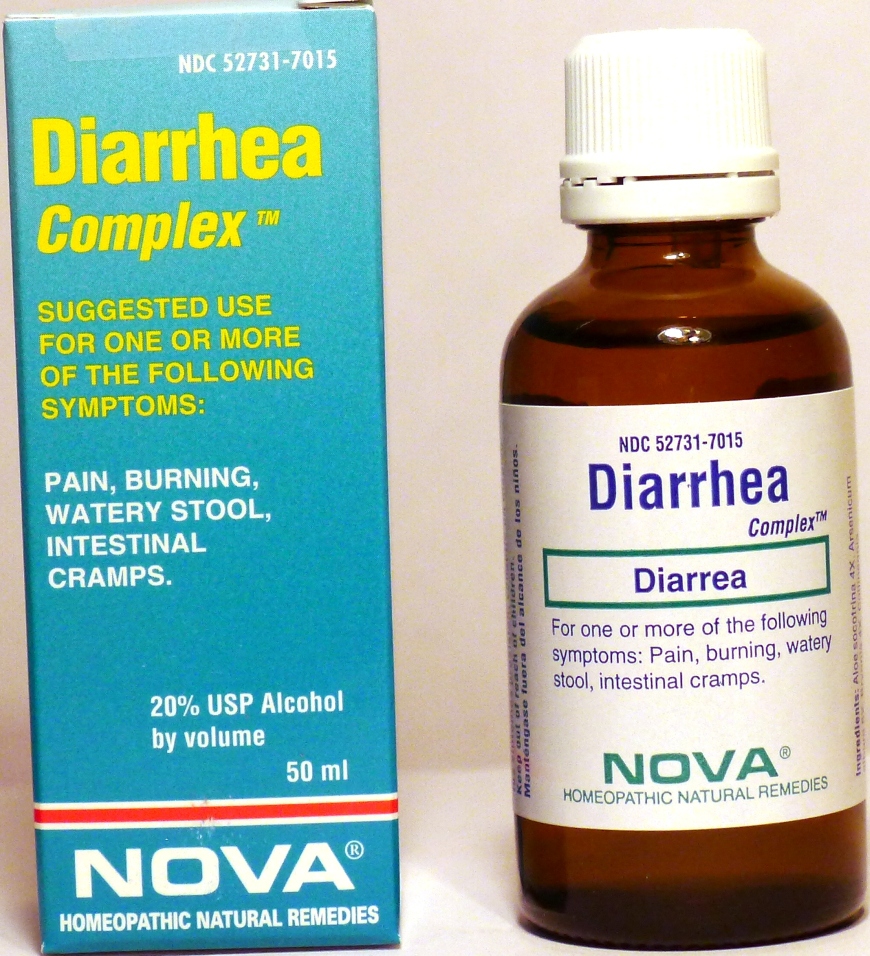 DRUG LABEL: Diarrhea Complex
NDC: 52731-7015 | Form: LIQUID
Manufacturer: Nova Homeopathic Therapeutics, Inc.
Category: homeopathic | Type: HUMAN OTC DRUG LABEL
Date: 20110601

ACTIVE INGREDIENTS: ALOE 4 [hp_X]/1 mL; ARSENIC TRIOXIDE 6 [hp_X]/1 mL; BRYONIA ALBA ROOT 4 [hp_X]/1 mL; COLLINSONIA CANADENSIS ROOT 3 [hp_X]/1 mL; CITRULLUS COLOCYNTHIS FRUIT PULP 4 [hp_X]/1 mL; CROTON TIGLIUM SEED 4 [hp_X]/1 mL; CUPRIC ACETATE 4 [hp_X]/1 mL; ECHINACEA ANGUSTIFOLIA 3 [hp_X]/1 mL; MERCURIC CHLORIDE 6 [hp_X]/1 mL; RHEUM OFFICINALE ROOT 3 [hp_X]/1 mL; SULFUR 8 [hp_X]/1 mL; VERATRUM ALBUM ROOT 4 [hp_X]/1 mL
INACTIVE INGREDIENTS: ALCOHOL

Diarrhea Complex

Purpose:

Suggested use for one or more of the following symptoms:

Pain, burning, watery stool, intestinal cramps.

Usage and Dosage:

For oral use only.

DOSAGE AND ADMINISTRATION

Adults:
In Acute Phase:
12-15 drops, every half hour until relief occurs
When Relief Occurs:
12-15 drops, 4-6 times per day
Children 2-12 years:
8-10 drops, 4-6 times per day
Infants 0-24 months:
4 drops, 4-6 times per day

Warnings:

Keep out of reach of children.

WARNINGS

If symptoms persist, consult a physician.
Do not use if ring on bottom of cap is broken or missing.

Active Ingredients:

Aloe socotrina 4X, Arsenicum album 6X, Bryonia 4X, Collinsonia canadensis 3X, Colocynthis 4X, Croton tiglium 4X, Cuprum aceticum 4X, Echinacea angustifolia 3X, Mercurius sub. corros 6X, Rheum officinale 3X, Sulfur 8X, Veratrum album 4X

Inactive Ingredients:

Alcohol, 20% USP

QUESTIONS

Manufactured by Nova Homeopathic Therapeutics Inc., Albuquerque, New Mexico USA 87109
1-800-225-8094

PACKAGE LABEL

Diarrhea Complex Product
Diarrhea Complex Bottle Label
Diarrhea Complex Box